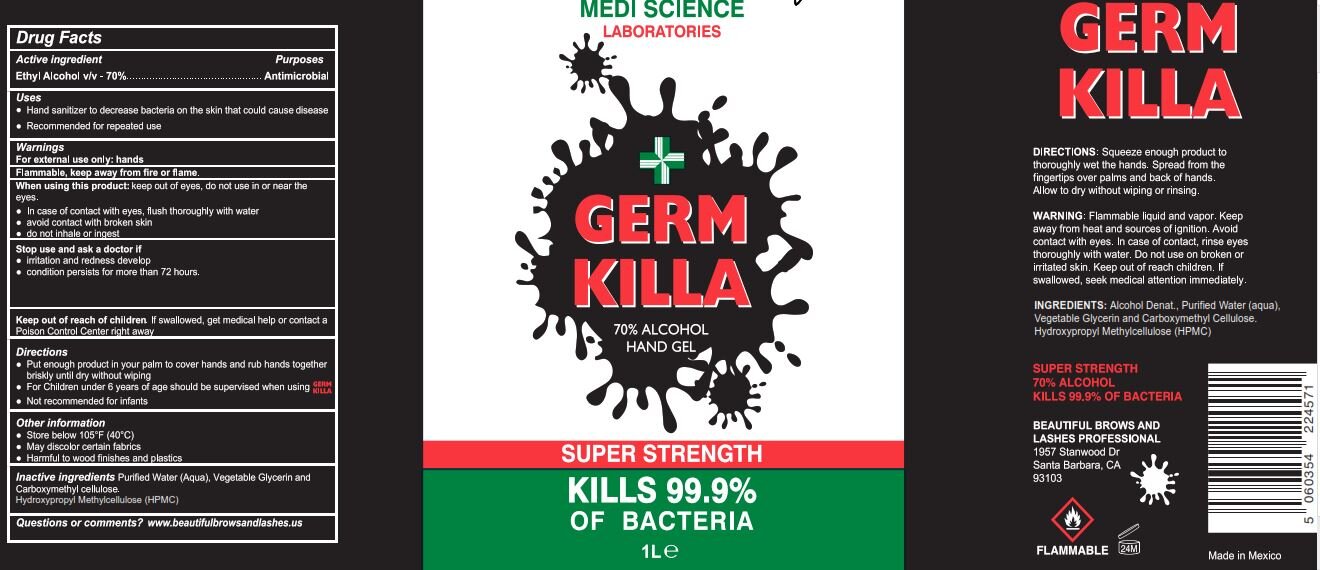 DRUG LABEL: HAND SANITIZER
NDC: 77210-0010 | Form: GEL
Manufacturer: EXPORTADORA IN & OUT S DE RL DE CV
Category: otc | Type: HUMAN OTC DRUG LABEL
Date: 20200616

ACTIVE INGREDIENTS: ALCOHOL 70 mL/100 mL
INACTIVE INGREDIENTS: HYPROMELLOSE 2208 (60000 MPA.S); WATER; CARBOXYMETHYLCELLULOSE; GLYCERIN

Active ingredient

ethyl alcohol v/v - 70%

purposes

antimicrobial

uses

hand sanitizer to decrease bacteria on the skin that could cause disease

recommended for repetead use

warnings

for external use only: hands

flammable, keep away from fire and flame

when using this product

keep out of eyes, do not use in or near the eyes

in case of contact with eyes, flush thorougly with water

avoid contact with broken skin

do not inhale or ingest

when using this product

keep out of eyes, do not use in or near the eyes

in case of contact with eyes, flush thorougly with water

avoid contact with broken skin

do not inhale or ingest

stop use and ask a doctor if

irritation and redness develo

condition persists for more than 72 hours

keep out of reach of children

if swallowed, get medical help or contact a posion control center right away

directions

put enough product in your palm to cover hands and rub hands together briskly until dry without wiping

for children under 6 years of age should be supervised when using germ killa

not recommended for infants

other information

store below 105 F (40C)

may discolor certain fabrics

harmful to wood finishes and plastics

inactive ingredients

purified water (aqua), vegetable glycerin and carboxymethyl cellulose, hydroxypropyl methylcellulose hpmc

principal display

medi science laboratories

germ killa

70% alcohol hand gel

super strenght

kills 99.9% of bacteria

1L